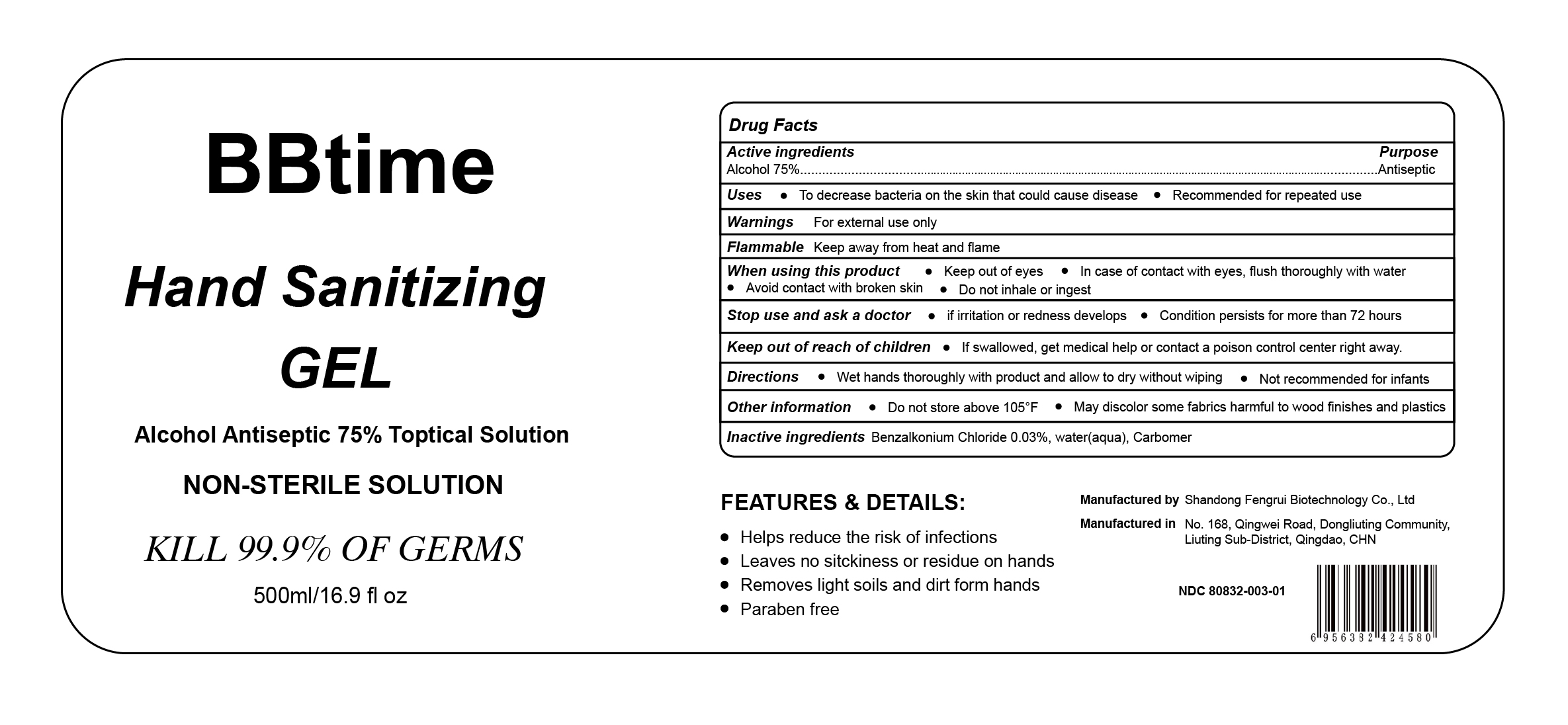 DRUG LABEL: BBtime Hand Sanitizing Gel
NDC: 80832-003 | Form: GEL
Manufacturer: Qingdao Fengrui Biotechnology Co., Ltd.
Category: otc | Type: HUMAN OTC DRUG LABEL
Date: 20201019

ACTIVE INGREDIENTS: ALCOHOL 75 mL/100 mL
INACTIVE INGREDIENTS: WATER; CARBOMER HOMOPOLYMER, UNSPECIFIED TYPE; BENZALKONIUM CHLORIDE

ACTIVE INGREDIENT

Alcohol 75%

PURPOSE

Antiseptic

Uses

To decrease bacteria on the skin that could cause disease

Recommended for repeated use

WARNINGS: For external use only

Flammable: Keep away form heat and flame

WHEN USING

Keep out of eyes

In case fo contact with thoroughly with water

Avoid contact with broken skin

Do not inhale or ingest

Stop use and ask a doctor

- if irritation or redness develops
- condition persists for more than 72 hours

KEEP OUT OF REACH OF CHILDREN

If swallowed, get medical help or contact a poison control center right away

Directions

Wet hands thoroughly with product and allow to dry without wiping

Not recommended for infants

Other information:

- Do not store above 105 ℉
- May discolor some fabrics harmful to wood finishes and plastics

INACTIVE INGREDIENT

Benzalkonium Chloride 0.03%, water(aqua)

Alcohol antiseptic 75% topical solution

NON-STERILE SOLUTION

KILL 99.9% OF GERMS

500ml/16.9 fl oz

FEATURES & DETAILS:

- Helps reduce the risk of infections
- Leaves no sitckiness or residue on hands
- Removes light soils and dirt form hands
- Paraben Free

Manufactured by Shandong Fengrui Biotechnology Co., Ltd.

Manufactured in No.168, Qingwei Road, Dongliuting Community, Liuting Sub-District, Qingdao,CHN

NDC 80832-003-01

PACKAGE LABEL

500ML NDC 80832-003-01